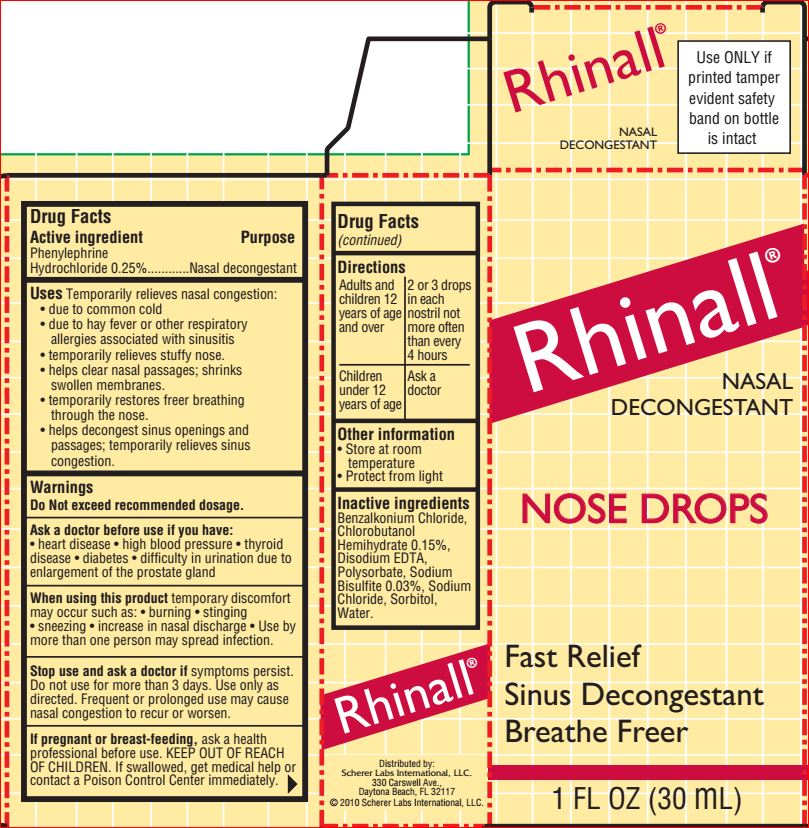 DRUG LABEL: Nasal Decongestant
NDC: 64048-5001 | Form: SOLUTION/ DROPS
Manufacturer: Product Quest Mfg.
Category: otc | Type: HUMAN OTC DRUG LABEL
Date: 20180620

ACTIVE INGREDIENTS: PHENYLEPHRINE HYDROCHLORIDE 0.25 g/100 mL
INACTIVE INGREDIENTS: BENZALKONIUM CHLORIDE; CHLOROBUTANOL HEMIHYDRATE; EDETATE DISODIUM; POLYSORBATE 20; SODIUM BISULFITE; SODIUM CHLORIDE; SORBITOL; WATER

Frug Facts

Active ingredient Purpose

Phenylephrine HCl 0.25%........Nasal decongestan

Uses

Temporarly relieves nasal congestion due to • common cold • hay fever or other respiratory allergies associated with sinusitis • stuffy nose
Helps clear nasal passages; shrinks swollen membranes.
Temporarily restores freer breathing through the nose.
Helps decongest sinus openings and passages; temporarily relieves sinus congestion.

Warnings

Do not exceed recommended dosage

Ask a doctor before use if you have: • heart disease • high blood pressure • diabetes• thyroid disease • difficulty in urination due to enlargement of the prostate gland

When using this product temporary discomfort may occur such as: • burning • stinging • sneezing • increase in nasal discharge • Use by more than one person may spread infection

Stop use and ask doctor if symptoms persist.

Do not use for more than 3 days. Use only as directed. Frequent or prolonged use may cause nasal congestion to recur or worsen.
If pregnant or breastfeeding, ask a health care professional before use.

KEEP OUT OF THE REACH OF CHILDREN. If swallowed, get medical help or contact a Poison Control Center immediately.

Directions

Adults and children 12 years of age and over: 2 or 3 drops in each nostril not more often than every 4 hours. Children under 12 years of age: ask a doctor.

Inactive ingredients

Benzalkonium Chloride, Chlorobutanol Hemihydrate, Disodium EDTA, Polysorbate, Sodium Bisulfite, Sodium Chloride, Sorbitol, Water.